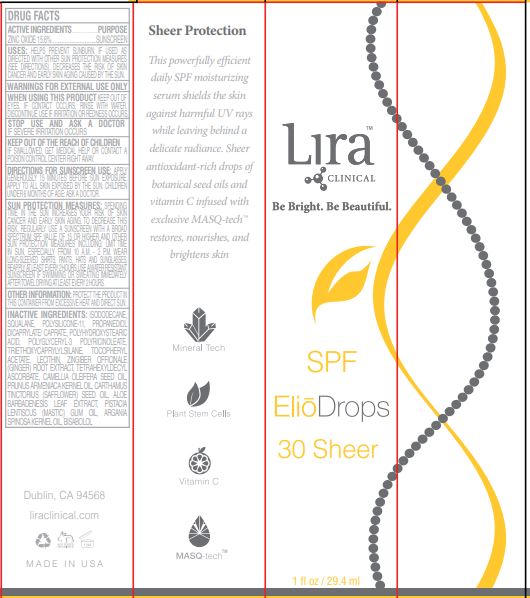 DRUG LABEL: SPF Elio Drops 30 Sheer
NDC: 62742-4232 | Form: CREAM
Manufacturer: Allure Labs Inc
Category: otc | Type: HUMAN OTC DRUG LABEL
Date: 20231028

ACTIVE INGREDIENTS: ZINC OXIDE 15.6 g/100 g
INACTIVE INGREDIENTS: ISODODECANE; ARGAN OIL; DIMETHICONE/VINYL DIMETHICONE CROSSPOLYMER (SOFT PARTICLE); LEVOMENOL; SQUALANE; POLYGLYCERYL-3 PENTARICINOLEATE; TETRAHEXYLDECYL ASCORBATE; PISTACIA LENTISCUS RESIN OIL; PROPANEDIOL DICAPRYLATE/CAPRATE; APRICOT KERNEL OIL; POLYHYDROXYSTEARIC ACID (2300 MW); TRIETHOXYCAPRYLYLSILANE; LECITHIN, SOYBEAN; SAFFLOWER OIL; ALOE VERA LEAF; .ALPHA.-TOCOPHEROL ACETATE; GINGER; CAMELLIA OIL

Drug Facts

ACTIVE INGREDIENTS - ZINC OXIDE 15.6%

PURPOSE...............SUNSCREEN

INDICATIONS AND USAGE

USES: HELPS PREVENT SUNBURN. IF USED AS DIRECTED WITH OTHER SUN PROTECTION MEASURES (SEE DIRECTIONS), DECREASES THE RISK OF SKIN CANCER AND EARLY SKIN AGING CAUSED BY THE SUN

WARNINGS FOR EXTERNAL USE ONLY

DISCONTINUE USE IF IRRITATION OR REDNESS OCCURS

WHEN USING THIS PRODUCT KEEP OUT OF EYES. IF CONTACT OCCURS, RINSE WITH WATER.

STOP USE AND ASK A DOCTOR IF SEVERE IRRITATION OCCURS

KEEP OUT OF REACH OF CHILDREN

KEEP OUT OF THE REACH OF CHILDREN IF SWALLOWED, GET MEDICAL HELP OR CONTACT A POISON CONTROL CENTER RIGHT AWAY.

DOSAGE AND ADMINISTRATION

DIRECTIONS FOR SUNSCREEN USE: APPLY GENEROUSLY 15 MINUTES BEFORE SUN EXPOSURE. APPLY TO ALL SKIN EXPOSED BY THE SUN. CHILDREN UNDER 6 MONTHS OF AGE: ASK A DOCTOR

SUN PROTECTION MEASURES: SPENDING TIME IN THE SUN INCREASES YOUR RISK OF SKIN CANCER AND EARLY SKIN AGING. TO DECREASE THIS RISK, REGULARLY USE A SUNSCREEN WITH A BROAD SPECTRUM SPF VALUE OF 15 OR HIGHER AND OTHER SUN PROTECTION MEASURES INCLUDING: LIMIT TIME IN SUN, ESPECIALLY FROM 10 A.M. - 2 P.M. WEAR LONG-SLEEVED SHIRTS, PANTS, HATS AND SUNGLASSES. REAPPLY AT LEAST EVERY 2 HOURS. USE A WATER RESISTANT SUNSCREEN IF SWIMMING OR SWEATING IMMEDIATELY AFTER TOWEL DRYING AT LEAST EVERY 2 HOURS.

OTHER INFORMATION:PROTECT THE PRODUCT IN THIS CONTAINER FROM EXCESSIVE HEAT AND DIRECT SUN

INACTIVE INGREDIENT

INACTIVE INGREDIENTS: ISODODECANE, SQUALANE, POLYSILICONE-11, PROPANEDIOL DICAPRYLATE/ CAPRATE, POLYHYDROXYSTEARIC ACID, POLYGLYCERYL-3 POLYRICINOLEATE, TRIETHOXYCAPRYLYLSILANE, TOCOPHERYL ACETATE, LECITHIN, ZINGIBER OFFICINALE (GINGER) ROOT EXTRACT, TETRAHEXYLDECYL ASCORBATE, CAMELLIA OLEIFERA SEED OIL, PRUNUS ARMENIACA KERNEL OIL, CARTHAMUS TINCTORIUS (SAFFLOWER) SEED OIL, ALOE BARBADENESIS LEAF EXTRACT, PISTACIA LENTISCUS (MASTIC) GUM OIL, ARGANIA SPINOSA KERNEL OIL, BISABOLOL